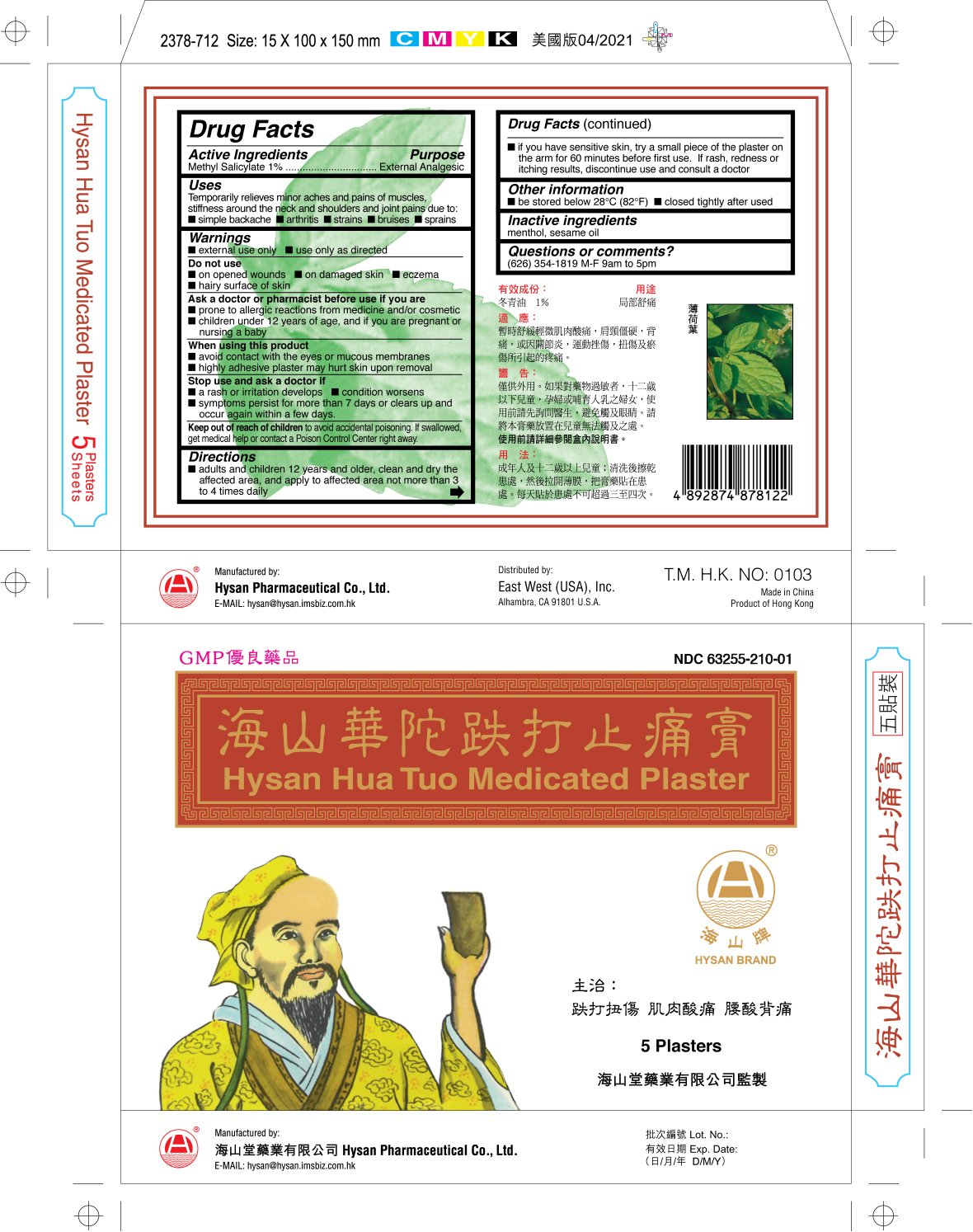 DRUG LABEL: HYSAN HUA TUO MEDICATED
NDC: 63255-210 | Form: PLASTER
Manufacturer: HYSAN PHARMACEUTICAL CO LTD
Category: otc | Type: HUMAN OTC DRUG LABEL
Date: 20241004

ACTIVE INGREDIENTS: METHYL SALICYLATE 1 g/1 1
INACTIVE INGREDIENTS: MENTHOL; SESAME OIL

Drug Facts

Active Ingredients

Methyl Salicylate 1%

Purpose

External Analgesic

Uses

Temporarily relieves minor aches and pains of muscles, stiffness around the neck and shoulders and joint pains due to:

- simple backache
- arthritis
- strains
- bruises
- sprains

Warnings

- external use only
- use only as directed

Do Not use

- on opened wounds
- on damaged skin
- eczema
- hairy surface of skin

Ask a doctor or pharmacist before use if you are

- prone to allergic reactions from medicine and/or cosmetic
- children under 12 years of age, and if you are pregnant or nursing a baby

When using this product

- avoid contact with the eyes or mucous membranes
- highly adhesive plaster may hurt skin upon removal

Stop use and ask a doctor if

- a rash or irritation develops
- condition worsens
- symptoms persist for more than 7 days or clears up and occur again within a few days

Keep out of reach of children to avoid accidental poisoning.

If swallowed, get medical help or contact a Poison Control Center right away

Directions

- adults and children 12 years and older, clean and dry the affected area, and apply to affected area not more than 3 to 4 times daily
- if you have sensitive skin, try a small piece of the plaster on the arm for 60 minutes before first use. If rash, redness or itching results, discontinue use and consult a doctor

Other information

- be stored below 28°C (82°F)
- closed tightly after used

Inactive ingredients

menthol, sesame Oil

Questions or comments?

(626) 354 1819 M-F 9am to 5pm